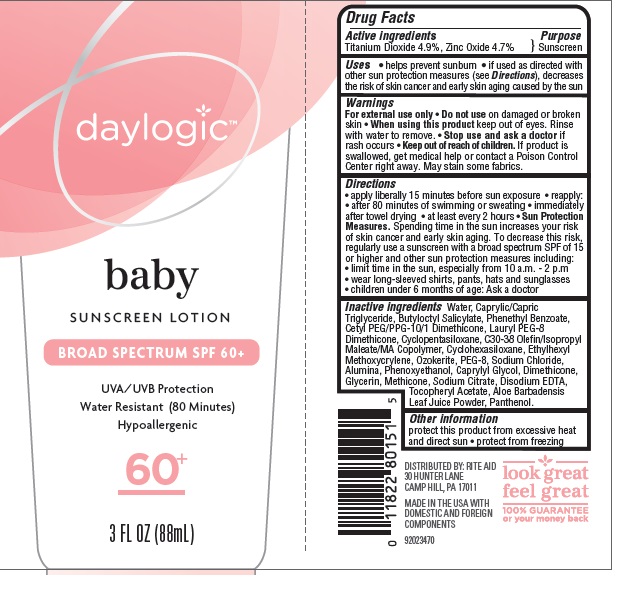 DRUG LABEL: Daylogic baby  SPF 60
NDC: 11822-3150 | Form: LOTION
Manufacturer: Rite Aid
Category: otc | Type: HUMAN OTC DRUG LABEL
Date: 20160308

ACTIVE INGREDIENTS: TITANIUM DIOXIDE 4.9 g/100 g; ZINC OXIDE  4.7 g/100 g
INACTIVE INGREDIENTS: WATER ; MEDIUM-CHAIN TRIGLYCERIDES; BUTYLOCTYL SALICYLATE; PHENETHYL BENZOATE; CYCLOMETHICONE 5; CYCLOMETHICONE 6; ETHYLHEXYL METHOXYCRYLENE; POLYETHYLENE GLYCOL 400; SODIUM CHLORIDE; ALUMINUM OXIDE; PHENOXYETHANOL; CAPRYLYL GLYCOL; DIMETHICONE; GLYCERIN; SODIUM CITRATE, UNSPECIFIED FORM; EDETATE DISODIUM; .ALPHA.-TOCOPHEROL ACETATE; ALOE VERA LEAF; PANTHENOL

Drug Facts

Active Ingredients

Titanium Dioxide 4.9%, Zinc Oxide 4.7%

Purpose

Sunscreen

Uses

• helps prevent sunburn

• if used as directed with other sun protection measures (see Directions), decreases the risk of skin cancer and early skin aging caused by the sun

Warnings

For external use only

Do not use

on damaged or broken skin

When using this product

keep out of eyes. Rinse with water to remove.

Stop use and ask a doctor

if rash occurs

Keep out of reach of children.

If product is swallowed, get medical help or contact a Poison Control Center right away.

• May stain some fabrics

Directions

• apply liberally 15 minutes before sun exposure

• reapply:

• after 80 minutes of swimming or sweating

• immediately after towel drying

• at least every 2 hours

Sun Protection Measures: Spending time in the sun increases your risk of skin cancer and early skin aging.

To decrease this risk, regularly use a sunscreen with a broad spectrum SPF of 15 or higher and other protection measures including:

• limit time in the sun, especially from 10 a.m. to 2 p.m.

• wear long-sleeved shirts, pants, hats, and sunglasses

• children under 6 months: Ask a doctor

Inactive Ingredients

Water, Caprylic/Capric Triglyceride, Butyloctyl Salicylate, Phenethyl Benzoate, Cetyl PEG/PPG-10/1 Dimethicone, Lauryl PEG-8 Dimethicone, Cyclopentasiloxane, C30-38 Olefin/Isopropyl aleate/MA Copolymer, Cyclohexasiloxane, Ethylhexyl Methoxycrylene, Ozokerite, PEG-8, Sodium Chloride, Alumina, Phenoxyethanol, Caprylyl Glycol, Dimethicone, Glycerin, Methicone, Sodium Citrate, Disodium EDTA, Tocopheryl Acetate, Aloe Barbadensis Leaf Juice Powder, Panthenol.

Other Information

• protect this product from excessive heat and direct sun

• protect from freezing

Principle Display Label

NDC: 11822-3150-2

daylogic

baby

SUNSCREEN LOTION

BROAD SPECTRUM SPF 60+

UVA/UVB Protection

Water Resistant (80 Minutes)

Hypoallergenc

60+

3 FL OZ (88ml)